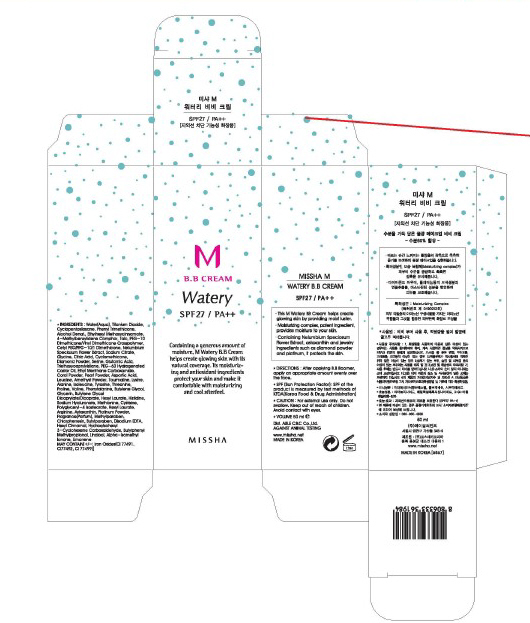 DRUG LABEL: MISSHA M WATERY B.B
NDC: 13733-001 | Form: CREAM
Manufacturer: ABLE C&C CO., LTD.
Category: otc | Type: HUMAN OTC DRUG LABEL
Date: 20100506

ACTIVE INGREDIENTS: TITANIUM DIOXIDE 3.57 mL/50 mL

Drug Facts

Active Ingredient: Titanium Dioxide

Inactive ingredients:

Water, Cyclopentasiloxane, Phenyl Trimethicone, Alcohol Denat, Ethylhexyl Methoxycinnamate, 4-Methylbenzylidene Camphor, Talc, PEG-10 Dimethicone/Vinyl, Dimethicone Crosspolymer, Cetyl PEG/PPG-10/1 Dimethicone, Nelumbium Speciosum Flower Extract, Iron Oxides, Sodium Citrate, Methylparaben, Chlorphenesin, Butylparaben, Glycine, Citric Acid, Fragrance, Cyclomethicone, Diamond Powder, Serine, Glutamic Acid, Triethoxycaprylylsilane, Disodium EDTA, PEG-60 Hydrogenated Castor Oil, Ethyl Menthane Carboxamide, Coral Powder, Pearl Powder, Aspartic Acid, Leucine, Amethyst Powder, Tourmaline, Lysine, Alanine, Isoleucine, Tyrosine, Threonine, Proline, Valine, Phenylalanine

PACKAGE LABEL

Directions : After applying B.B Boomer, apply an appropriate amount evenly over the face.

Caution :

For external use only.

Do not swallow.

Keep out of reach of children.

Avoid contact with eyes.